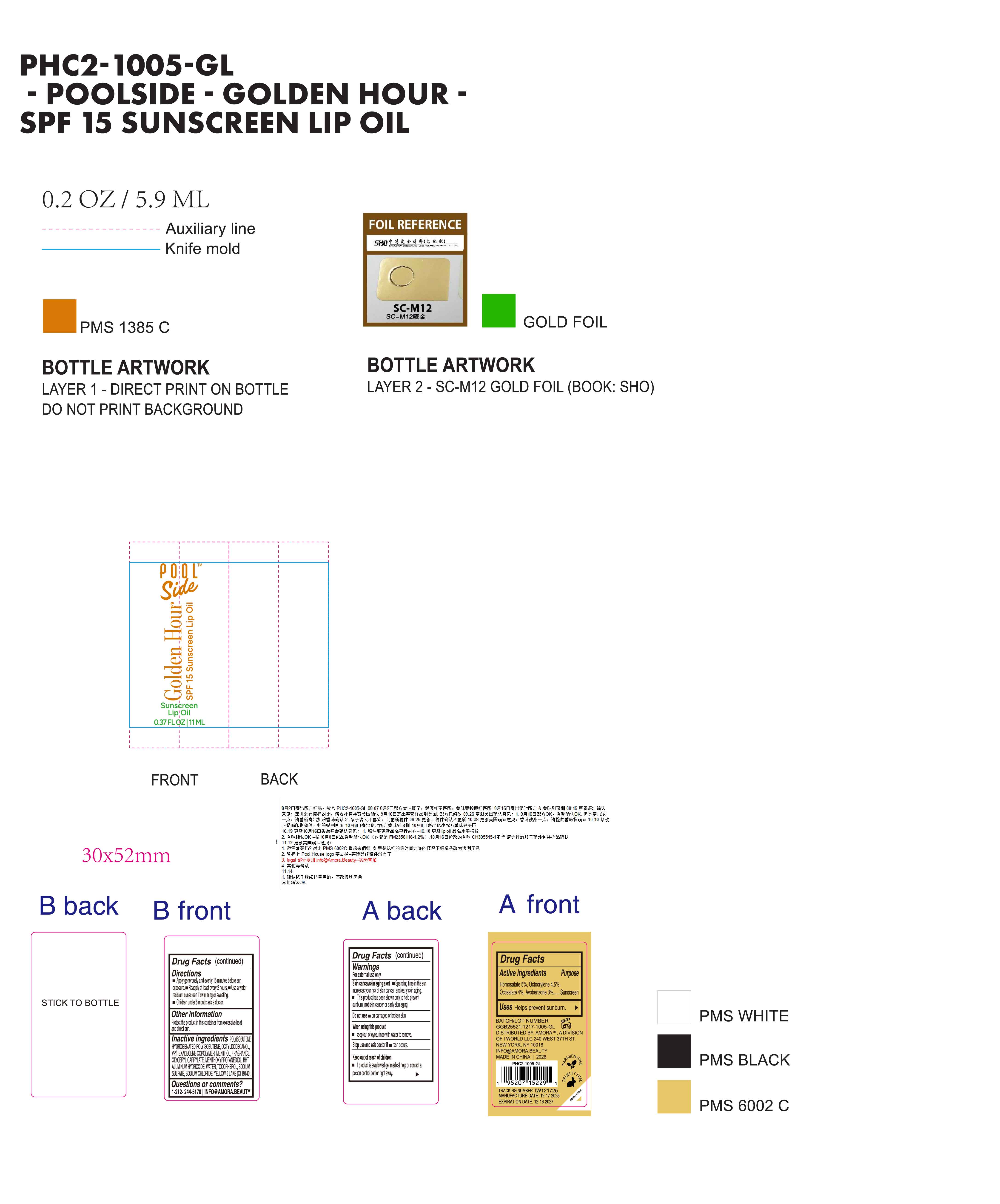 DRUG LABEL: Poolside Golden Hour SPF15 sunscreen lip oil
NDC: 85161-161 | Form: OIL
Manufacturer: Longway Technology(Guangzhou)Co.,Ltd.
Category: otc | Type: HUMAN OTC DRUG LABEL
Date: 20251204

ACTIVE INGREDIENTS: HOMOSALATE 0.05 g/1 mL; AVOBENZONE 0.03 g/1 mL; OCTOCRYLENE 0.045 g/1 mL; OCTISALATE 0.04 g/1 mL
INACTIVE INGREDIENTS: ALUMINUM HYDROXIDE; HYDROGENATED POLYISOBUTENE (450 MW); FRAGRANCE 13576; VP/HEXADECENE COPOLYMER; SODIUM CHLORIDE; GLYCERYL CAPRYLATE; CI 19140; TOCOPHEROL; BHT; WATER; SODIUM SULFATE; POLYISOBUTYLENE (1300 MW); OCTYLDODECANOL; MENTHOL; MENTHOXYPROPANEDIOL

ACTIVE INGREDIENT

Homosalate,Octocrylene,Octisalate,Avobenzone

KEEP OUT OF REACH OF CHILDREN

If product is swallowed get meditcal help or contact avpoison control center rnigh away.

QUESTIONS

1-212-244-5170| INFO@AMORA.BEAUTY

OTHER SAFETY INFORMATION

Protect the product in this container from excessive heat and direct sun.

WARNINGS

For external use only.

Skin cancer/skin aging alert.

Spending time in the sun increases your risk of skin cancer and early skin aging.

This product has been shown only to help prevent sunburn, not skin cancer or early skin aging.

Do not use on damaged or broken skin.

When using this product.

keep out of eves. rinse with water to remove.

Stop use and ask doctor if rash occurs.

Keep out of reach of children.

lf product is swallowed get medical help or contact a poison control center right away

DOSAGE AND ADMINISTRATION

Apply generously and evenly 15 minuies before sun exposure.

Reaply at least every 2 hour.

Use a water resistant sunscreen if swimming or sweating.

Children under 6 month: ask a doctor.

INDICATIONS AND USAGE

Helps prevent sunburn.

INACTIVE INGREDIENT

POLYISOBUTENE,HYDROGENATED POLYISOBUTENE,OCTYLDODECANOL,VP/HEXADECENE COPOLYMER,MENTHOL,FRAGRANCE,GLYCERYL CAPRYLATE,MENTHOXYPROPANEDIOL,BHT,ALUMINUM HYDROXIDE,WATER,TOCOPHEROL,SODIUM SULFATE,SODIUM CHLORIDE,YELLOW 5 LAKE(CI 45410)

PURPOSE

Sunscreen